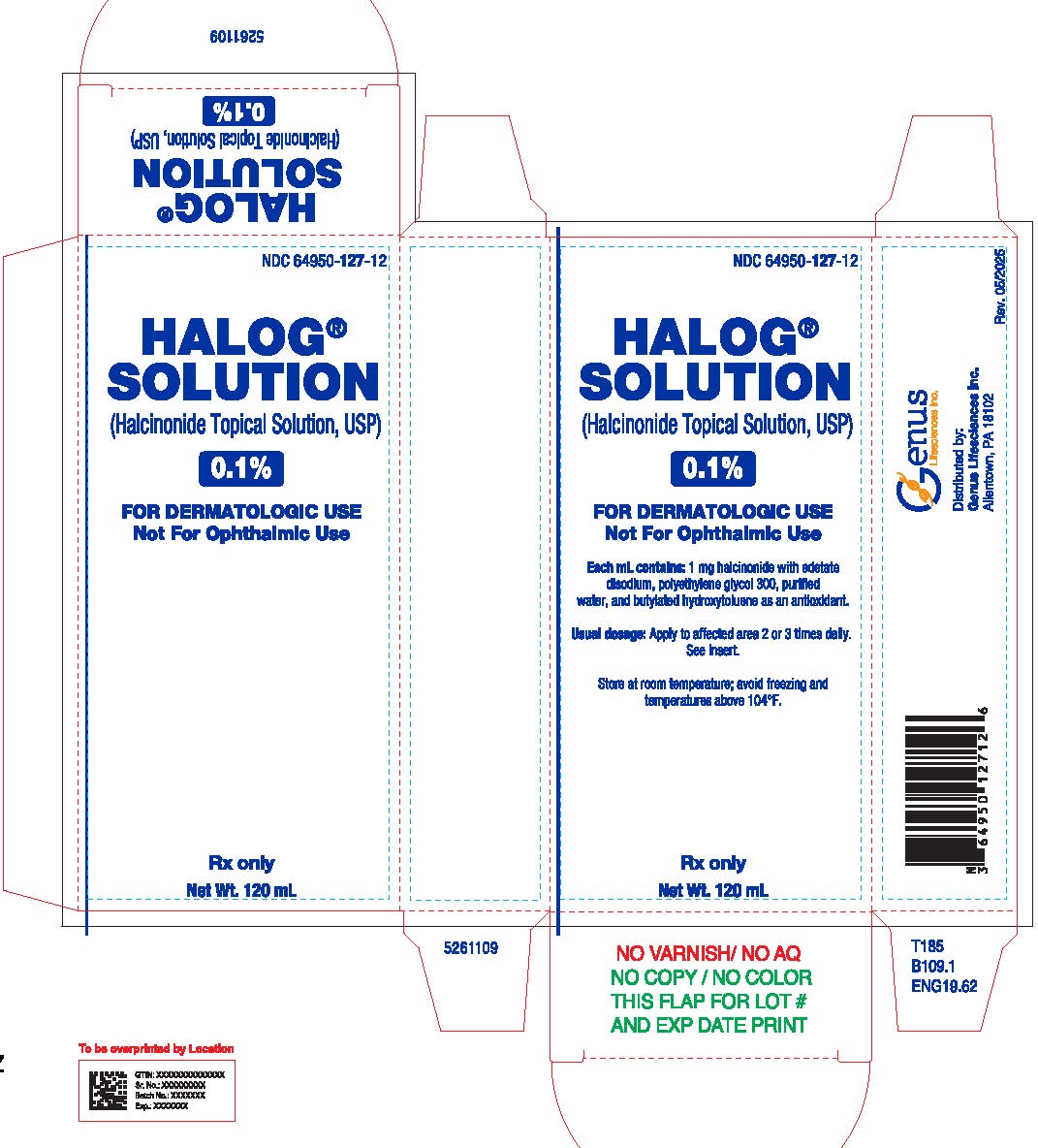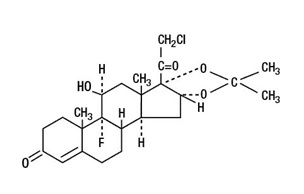 DRUG LABEL: HALOG
NDC: 64950-127 | Form: SOLUTION
Manufacturer: Genus Lifesciences Inc.
Category: prescription | Type: HUMAN PRESCRIPTION DRUG LABEL
Date: 20251105

ACTIVE INGREDIENTS: HALCINONIDE 1 mg/1 mL
INACTIVE INGREDIENTS: BUTYLATED HYDROXYTOLUENE; EDETATE DISODIUM; POLYETHYLENE GLYCOL 300; WATER

Halcinonide Topical Solution, USP 0.1%
For Topical Use Only. Not For Ophthalmic Use.

Rx Only

DESCRIPTION

The topical corticosteroids constitute a class of primarily synthetic steroids used as anti- inflammatory and antipruritic agents. The steroids in this class include halcinonide. Halcinonide is designated chemically as 21-Chloro-9-fluoro-11β, 16α, 17-trihydroxypregn-4-ene-3, 20-dione cyclic 16, 17-acetal with acetone. Structural formula:

C24H32ClFO5, MW 454.96, CAS-3093-35-4

Each mL of 0.1% HALOG SOLUTION (Halcinonide Topical Solution, USP) contains 1 mg halcinonide, edetate disodium, polyethylene glycol 300, and purified water with butylated hydroxytoluene as an antioxidant.

CLINICAL PHARMACOLOGY

Topical corticosteroids share anti-inflammatory, antipruritic and vasoconstrictive actions.
The mechanism of anti-inflammatory activity of the topical corticosteroids is unclear. Various laboratory methods, including vasoconstrictor assays, are used to compare and predict potencies and/or clinical efficacies of the topical corticosteroids. There is some evidence to suggest that a recognizable correlation exists between vasoconstrictor potency and therapeutic efficacy in man.

Pharmacokinetics
The extent of percutaneous absorption of topical corticosteroids is determined by many factors including the vehicle, the integrity of the epidermal barrier, and the use of occlusive dressings.
Topical corticosteroids can be absorbed from normal intact skin. Inflammation and/or other disease processes in the skin increase percutaneous absorption. Occlusive dressings substantially increase the percutaneous absorption of topical corticosteroids. Thus, occlusive dressings may be a valuable therapeutic adjunct for treatment of resistant dermatoses (see DOSAGE AND ADMINISTRATION).
Once absorbed through the skin, topical corticosteroids are handled through pharmacokinetic pathways similar to systemically administered corticosteroids. Corticosteroids are bound to plasma proteins in varying degrees. Corticosteroids are metabolized primarily in the liver and are then excreted by the kidneys. Some of the topical corticosteroids and their metabolites are also excreted into the bile.

INDICATIONS AND USAGE

HALOG SOLUTION (Halcinonide Topical Solution, USP) 0.1% is indicated for the relief of the inflammatory and pruritic manifestations of corticosteroid-responsive dermatoses.

CONTRAINDICATIONS

Topical corticosteroids are contraindicated in those patients with a history of hypersensitivity to any of the components of the preparations.

PRECAUTIONS

General

Systemic absorption of topical corticosteroids has produced reversible hypothalamic- pituitary-adrenal (HPA) axis suppression, manifestations of Cushing’s syndrome, hyperglycemia, and glucosuria in some patients.
Conditions which augment systemic absorption include the application of the more potent steroids, use over large surface areas, prolonged use, and the addition of occlusive dressings.

Therefore, patients receiving a large dose of any potent topical steroid applied to a large surface area or under an occlusive dressing should be evaluated periodically for evidence of HPA axis suppression by using the urinary free cortisol and ACTH stimulation tests, and for impairment of thermal homeostasis. If HPA axis suppression or elevation of the body temperature occurs, an attempt should be made to withdraw the drug, to reduce the frequency of application, substitute a less potent steroid, or use a sequential approach when utilizing the occlusive technique.
Recovery of HPA axis function and thermal homeostasis are generally prompt and complete upon discontinuation of the drug. Infrequently, signs and symptoms of steroid withdrawal may occur, requiring supplemental systemic corticosteroids. Occasionally, a patient may develop a sensitivity reaction to a particular occlusive dressing material or adhesive and a substitute material may be necessary.
Children may absorb proportionally larger amounts of topical corticosteroids and thus be more susceptible to systemic toxicity (see PRECAUTIONS: Pediatric Use).
If irritation develops, topical corticosteroids should be discontinued and appropriate therapy instituted.
In the presence of dermatological infections, the use of an appropriate antifungal or antibacterial agent should be instituted. If a favorable response does not occur promptly, the corticosteroid should be discontinued until the infection has been adequately controlled.
This preparation is not for ophthalmic use.

Information for the Patient

Patients using topical corticosteroids should receive the following information and instructions:
1) This medication is to be used as directed by the physician. It is for dermatologic use only. Avoid contact with the eyes.
2) Patients should be advised not to use this medication for any disorder other than for which it was prescribed.
3) The treated skin area should not be bandaged or otherwise covered or wrapped as to be occlusive unless directed by the physician.
4) Patients should report any signs of local adverse reactions especially under occlusive dressing.
5) Parents of pediatric patients should be advised not to use tight-fitting diapers or plastic pants on a child being treated in the diaper area, as these garments may constitute occlusive dressings.

Laboratory Tests

A urinary free cortisol test and ACTH stimulation test may be helpful in evaluating HPA axis suppression.

Carcinogenesis, Mutagenesis, and Impairment of Fertility

Long-term animal studies have not been performed to evaluate the carcinogenic potential or the effect on fertility of topical corticosteroids.

Studies to determine mutagenicity with prednisolone and hydrocortisone showed negative results.

Pregnancy

Teratogenic Effects
Corticosteroids are generally teratogenic in laboratory animals when administered systemically at relatively low dosage levels. The more potent corticosteroids have been shown to be teratogenic after dermal application in laboratory animals. There are no adequate and well-controlled studies in pregnant women on teratogenic effects from topically applied corticosteroids. Therefore, topical corticosteroids should be used during pregnancy only if the potential benefit justifies the potential risk to the fetus. Drugs of this class should not be used extensively on pregnant patients, in large amounts, or for prolonged periods of time.

Nursing Mothers

It is not known whether topical administration of corticosteroids could result in sufficient systemic absorption to produce detectable quantities in breast milk. Systemically administered corticosteroids are secreted into breast milk in quantities not likely to have a deleterious effect on the infant. Nevertheless, caution should be exercised when topical corticosteroids are administered to a nursing woman.

Pediatric Use

Pediatric patients may demonstrate greater susceptibility to topical corticosteroid- induced HPA axis suppression and Cushing’s syndrome than mature patients because of a larger skin surface area to body weight ratio.

HPA axis suppression, Cushing’s syndrome, and intracranial hypertension have been reported in children receiving topical corticosteroids. Manifestations of adrenal suppression in children include linear growth retardation, delayed weight gain, low plasma cortisol levels, and absence of response to ACTH stimulation. Manifestations of intracranial hypertension include bulging fontanelles, headaches, and bilateral papilledema.

Administration of topical corticosteroids to children should be limited to the least amount compatible with an effective therapeutic regimen. Chronic corticosteroid therapy may interfere with the growth and development of children.

Geriatric Use

Clinical studies of 0.1% HALOG SOLUTION (Halcinonide Topical Solution, USP) did not include sufficient numbers of patients aged 65 years and over to determine whether they respond differently from younger patients. Other reported clinical experience has not identified differences in responses between the elderly and younger patients. In general, dose selection for an elderly patient should be cautious, usually starting at the low end of the dosing range.

ADVERSE REACTIONS

The following local adverse reactions are reported infrequently with topical corticosteroids, but may occur more frequently with the use of occlusive dressings (reactions are listed in an approximate decreasing order of occurrence): burning, itching, irritation, dryness, folliculitis, hypertrichosis, acneiform eruptions, hypopigmentation, perioral dermatitis, allergic contact dermatitis, maceration of the skin, secondary infection, skin atrophy, striae, and miliaria.

OVERDOSAGE

Topically applied corticosteroids can be absorbed in sufficient amounts to produce systemic effects (see PRECAUTIONS: General).

DOSAGE AND ADMINISTRATION

Apply HALOG SOLUTION (Halcinonide Topical Solution, USP) 0.1% to the affected area two to three times daily.
Occlusive Dressing Technique

Occlusive dressings may be used for the management of psoriasis or other recalcitrant conditions. Apply the solution to the lesion, cover with a pliable nonporous film, and seal the edges. If needed, additional moisture may be provided by covering the lesion with a dampened clean cotton cloth before the nonporous film is applied or by briefly wetting the affected area with water immediately prior to applying the medication. The frequency of changing dressings is best determined on an individual basis. It may be convenient to apply Halcinonide Topical Solution, USP 0.1% under an occlusive dressing in the evening and to remove the dressing in the morning (i.e., 12-hour occlusion). When utilizing the 12-hour occlusion regimen, additional solution should be applied, without occlusion, during the day. Reapplication is essential at each dressing change.
If an infection develops, the use of occlusive dressings should be discontinued and appropriate antimicrobial therapy instituted.

HOW SUPPLIED

HALOG® SOLUTION (Halcinonide Topical Solution, USP) 0.1% is supplied in plastic squeeze bottles containing 120 mL (NDC 64950-127-12) of solution.

Storage
Store at room temperature; avoid freezing and temperatures above 104° F.

To report SUSPECTED ADVERSE REACTIONS, contact Allucent at 1-866-511-6754 or FDA at 1-800-FDA-1088 or www.fda.gov/medwatch.

Distributed by:
Genus Lifesciences Inc.
Allentown, PA 18102

Revised: May 2025
5261181
50

PACKAGE LABEL.PRINCIPAL DISPLAY PANEL

NDC 64950-127-12

HALOG® SOLUTION (Halcinonide Topical Solution, USP 0.1%)

FOR DERMATOLOGIC USE

Not For Ophthalmic Use

Net Wt. 120 ml

Rx only